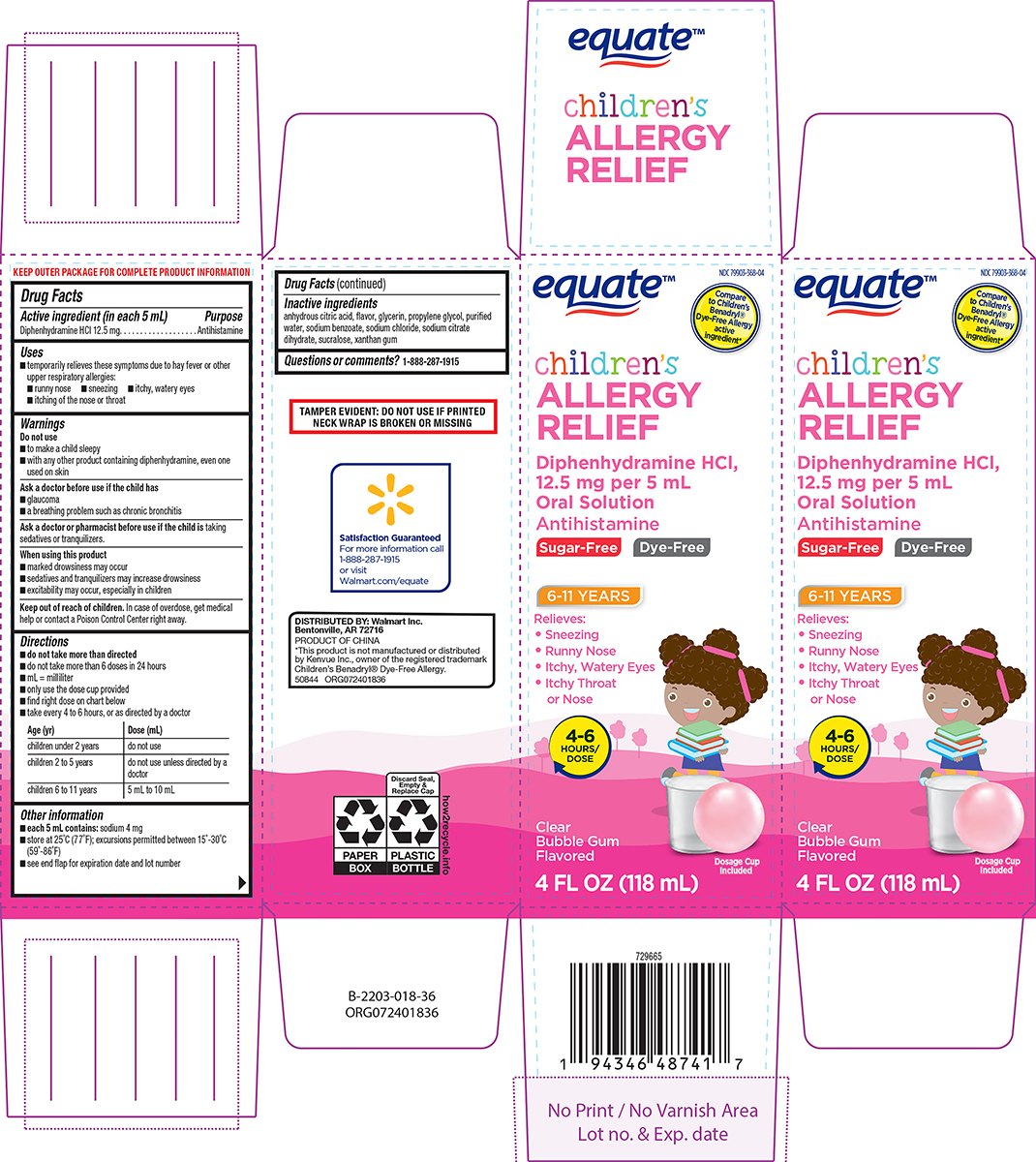 DRUG LABEL: Allergy Relief
NDC: 79903-368 | Form: SOLUTION
Manufacturer: WALMART INC.
Category: otc | Type: HUMAN OTC DRUG LABEL
Date: 20250619

ACTIVE INGREDIENTS: DIPHENHYDRAMINE HYDROCHLORIDE 12.5 mg/5 mL
INACTIVE INGREDIENTS: ANHYDROUS CITRIC ACID; GLYCERIN; PROPYLENE GLYCOL; WATER; SODIUM BENZOATE; SODIUM CHLORIDE; TRISODIUM CITRATE DIHYDRATE; SUCRALOSE; XANTHAN GUM

Equate 44-018 RESERVED 79903-368

Active ingredient (in each 5 mL)

Diphenhydramine HCl 12.5 mg

Purpose

Antihistamine

Uses

- temporarily relieves these symptoms due to hay fever or other upper respiratory allergies:
  - runny nose
  - sneezing
  - itchy, watery eyes
  - itching of the nose or throat

Warnings

Do not use

- to make a child sleepy
- with any other product containing diphenhydramine, even one used on skin

Ask a doctor before use if the child has

- glaucoma
- a breathing problem such as chronic bronchitis

Ask a doctor or pharmacist before use if the child is

taking sedatives or tranquilizers.

When using this product

- marked drowsiness may occur
- sedatives and tranquilizers may increase drowsiness
- excitability may occur, especially in children

Keep out of reach of children.

In case of overdose, get medical help or contact a Poison Control Center right away.

Directions

- do not take more than directed
- do not take more than 6 doses in 24 hours
- mL = milliliter
- only use the dose cup provided
- find right dose on chart below
- take every 4 to 6 hours, or as directed by a doctor

Age (yr) | Dose (mL)
children under 2 years | do not use
children 2 to 5 years | do not use unless directed by a doctor
children 6 to 11 years | 5 mL to 10 mL

Other information

- each 5 mL contains: sodium 4 mg
- store at 25°C (77°F); excursions permitted between 15°-30°C (59°-86°F)
- see end flap for expiration date and lot number

Inactive ingredients

anhydrous citric acid, flavor, glycerin, propylene glycol, purified water, sodium benzoate, sodium chloride, sodium citrate dihydrate, sucralose, xanthan gum

Questions or comments?

1-888-287-1915

Principal Display Panel

equate™

NDC 79903-368-04

Compare
to Children’s
Benadryl®
Dye-Free Allergy
active
ingredient*

children's
ALLERGY
RELIEF

Diphenhydramine HCl,
12.5 mg per 5 mL
Oral Solution
Antihistamine

Sugar-Free
Dye-Free

6-11 YEARS

Relieves:
• Sneezing
• Runny Nose
• Itchy, Watery Eyes
• Itchy Throat
or Nose

4-6
HOURS/
DOSE

Clear
Bubble Gum
Flavored

Dosage Cup
Included

4 FL OZ (118 mL)

TAMPER EVIDENT: DO NOT USE IF PRINTED
NECK WRAP IS BROKEN OR MISSING

DISTRIBUTED BY: Walmart Inc.
Bentonville, AR 72716
PRODUCT OF CHINA
*This product is not manufactured or distributed
by Kenvue Inc., owner of the registered trademark
Children’s Benadryl® Dye-Free Allergy.
50844 ORG072401836

Equate 44-018